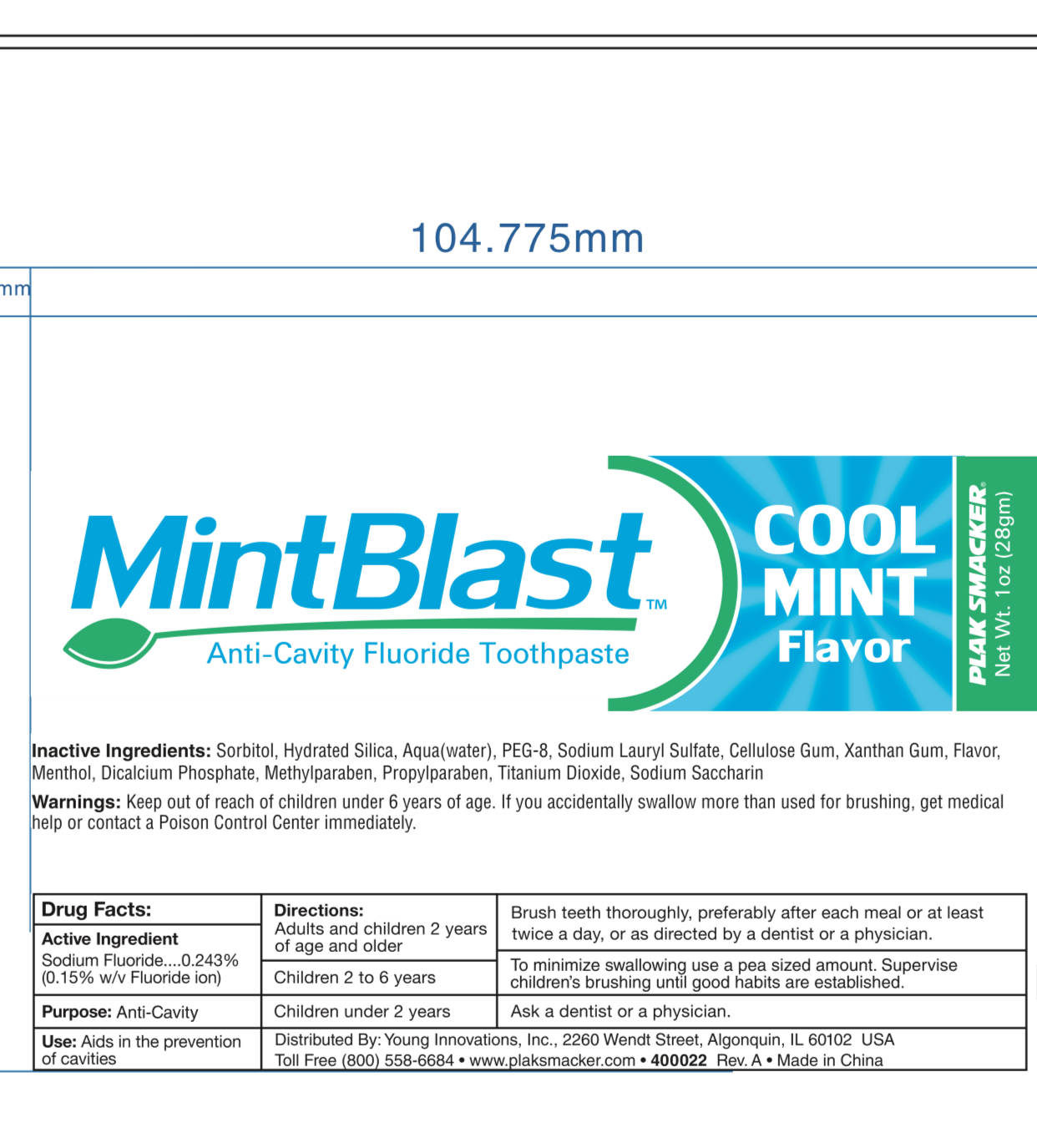 DRUG LABEL: MintBlast Cool Mint Flavor Anti Cavity Fluoride Tooth
NDC: 70766-006 | Form: PASTE, DENTIFRICE
Manufacturer: Yangzhou SION Commodity Co.,Ltd
Category: otc | Type: HUMAN OTC DRUG LABEL
Date: 20231208

ACTIVE INGREDIENTS: SODIUM FLUORIDE 0.15 g/100 g
INACTIVE INGREDIENTS: WATER; SORBITOL; XANTHAN GUM; HYDRATED SILICA; SODIUM LAURYL SULFATE; MENTHOL; CALCIUM PHOSPHATE, DIBASIC, ANHYDROUS; METHYLPARABEN; PROPYLPARABEN; TITANIUM DIOXIDE; SACCHARIN SODIUM

Mintblast Cool Mint Flavor Fluoride Toothpaste

Active ingredients

SODIUM FLUORIDE 0.24%(0.1 w/v Fluoride ion)

Purpose

anticavity

Uses

aids in the prevention of cavities.

Warnings

Keep out of the reach of children under 6 years of age. If accidently swallow more than used for brushing,get medical help or contact a Poison Control Center immediately.

Keep out of reach of children.

Directions

Adults and children 2 years of age and older:

Brush teeth thoroughly, preferrably after each meal or at least twice a day, or as directed by a dentist or a physician

Children two to six years:

To minimize swallowing, use a pea sized amount. Supervise children brushing until good habits are estabished.

Chidren under two years:

Ask a dentist or a physician

INACTIVE INGREDIENT

Sorbitol, Hydrated silica,Water, PEG-8, Sodium lauryl sulfate, Cellulose gum, Xanthan gum, flavor, Menthol, Dicalcium Phosphate, Methylparaben, Propylparaben, Titanium Dioxide, sodium sacharine